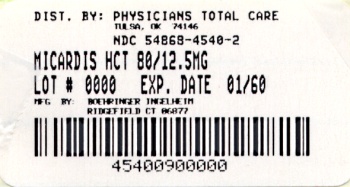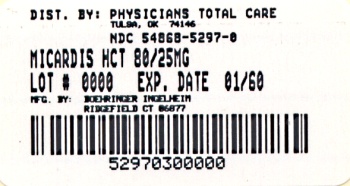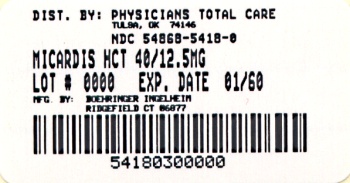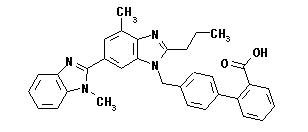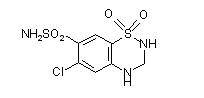 DRUG LABEL: Micardis HCT
NDC: 54868-5418 | Form: TABLET
Manufacturer: Physicians Total Care, Inc.
Category: prescription | Type: HUMAN PRESCRIPTION DRUG LABEL
Date: 20120214

ACTIVE INGREDIENTS: TELMISARTAN 40 mg/1 1; HYDROCHLOROTHIAZIDE 12.5 mg/1 1
INACTIVE INGREDIENTS: SODIUM HYDROXIDE; MEGLUMINE; POVIDONE; SORBITOL; MAGNESIUM STEARATE; LACTOSE MONOHYDRATE; CELLULOSE, MICROCRYSTALLINE; STARCH, CORN; SODIUM STARCH GLYCOLATE TYPE A POTATO; FERRIC OXIDE RED

Micardis® HCT
(telmisartan and hydrochlorothiazide)
Tablets, 40 mg/12.5 mg
80 mg/12.5 mg and 80 mg/25 mg

Prescribing Information

WARNING: FETAL TOXICITY

- When pregnancy is detected, discontinue MICARDIS HCT as soon as possible.
- Drugs that act directly on the renin-angiotensin system can cause injury and death to the developing fetus (see WARNINGS, Fetal Toxicity).

DESCRIPTION

MICARDIS HCT tablets are a combination of telmisartan, an orally active angiotensin II antagonist acting on the AT1 receptor subtype, and hydrochlorothiazide, a diuretic.

Telmisartan, a non-peptide molecule, is chemically described as 4'-[(1,4'-dimethyl-2'-propyl[2,6'-bi-1H-benzimidazol]-1'-yl)methyl]-[1,1'-biphenyl]-2-carboxylic acid. Its empirical formula is C33H30N4O2, its molecular weight is 514.63, and its structural formula is:

Telmisartan is a white to slightly yellowish solid. It is practically insoluble in water and in the pH range of 3 to 9, sparingly soluble in strong acid (except insoluble in hydrochloric acid), and soluble in strong base.

Hydrochlorothiazide is a white, or practically white, practically odorless, crystalline powder with a molecular weight of 297.74. It is slightly soluble in water, and freely soluble in sodium hydroxide solution. Hydrochlorothiazide is chemically described as 6-chloro-3,4-dihydro-2H-1,2,4-benzothiadiazine-7-sulfonamide 1,1-dioxide. Its empirical formula is C7H8ClN3O4S2, and its structural formula is:

MICARDIS HCT tablets are formulated for oral administration in three combinations of 40 mg/12.5 mg, 80 mg/12.5 mg, and 80 mg/25 mg telmisartan and hydrochlorothiazide, respectively. The tablets contain the following inactive ingredients: sodium hydroxide, meglumine, povidone, sorbitol, magnesium stearate, lactose monohydrate, microcrystalline cellulose, maize starch, sodium starch glycolate. As coloring agents, the 40 mg/12.5 mg and 80 mg/12.5 mg tablets contain ferric oxide red, and the 80 mg/25 mg tablets contain ferric oxide yellow. Micardis® HCT (telmisartan and hydrochlorothiazide) tablets are hygroscopic and require protection from moisture.

CLINICAL PHARMACOLOGY

Mechanism of Action

Angiotensin II is formed from angiotensin I in a reaction catalyzed by angiotensin-converting enzyme (ACE, kininase II). Angiotensin II is the principal pressor agent of the renin-angiotensin system, with effects that include vasoconstriction, stimulation of synthesis and release of aldosterone, cardiac stimulation, and renal reabsorption of sodium. Telmisartan blocks the vasoconstrictor and aldosterone-secreting effects of angiotensin II by selectively blocking the binding of angiotensin II to the AT1 receptor in many tissues, such as vascular smooth muscle and the adrenal gland. Its action is therefore independent of the pathways for angiotensin II synthesis.

There is also an AT2 receptor found in many tissues, but AT2 is not known to be associated with cardiovascular homeostasis. Telmisartan has much greater affinity (>3,000 fold) for the AT1 receptor than for the AT2 receptor.

Blockade of the renin-angiotensin system with ACE inhibitors, which inhibit the biosynthesis of angiotensin II from angiotensin I, is widely used in the treatment of hypertension. ACE inhibitors also inhibit the degradation of bradykinin, a reaction also catalyzed by ACE. Because telmisartan does not inhibit ACE (kininase II), it does not affect the response to bradykinin. Whether this difference has clinical relevance is not yet known. Telmisartan does not bind to or block other hormone receptors or ion channels known to be important in cardiovascular regulation.

Blockade of the angiotensin II receptor inhibits the negative regulatory feedback of angiotensin II on renin secretion, but the resulting increased plasma renin activity and angiotensin II circulating levels do not overcome the effect of telmisartan on blood pressure.

Hydrochlorothiazide is a thiazide diuretic. Thiazides affect the renal tubular mechanisms of electrolyte reabsorption, directly increasing excretion of sodium salt and chloride in approximately equivalent amounts. Indirectly, the diuretic action of hydrochlorothiazide reduces plasma volume, with consequent increases in plasma renin activity, increases in aldosterone secretion, increases in urinary potassium loss, and decreases in serum potassium. The renin-aldosterone link is mediated by angiotensin II, so coadministration of an angiotensin II receptor antagonist tends to reverse the potassium loss associated with these diuretics.

The mechanism of the antihypertensive effect of thiazides is not fully understood.

Pharmacokinetics

General

Telmisartan

Following oral administration, peak concentrations (Cmax) of telmisartan are reached in 0.5-1 hour after dosing. Food slightly reduces the bioavailability of telmisartan, with a reduction in the area under the plasma concentration-time curve (AUC) of about 6% with the 40 mg tablet and about 20% after a 160 mg dose. The absolute bioavailability of telmisartan is dose dependent. At 40 and 160 mg the bioavailability was 42% and 58%, respectively. The pharmacokinetics of orally administered telmisartan are nonlinear over the dose range 20-160 mg, with greater than proportional increases of plasma concentrations (Cmax and AUC) with increasing doses. Telmisartan shows bi-exponential decay kinetics with a terminal elimination half-life of approximately 24 hours. Trough plasma concentrations of telmisartan with once daily dosing are about 10-25% of peak plasma concentrations. Telmisartan has an accumulation index in plasma of 1.5 to 2.0 upon repeated once daily dosing.

Hydrochlorothiazide

When plasma levels have been followed for at least 24 hours, the plasma half-life has been observed to vary between 5.6 and 14.8 hours.

Metabolism and Elimination

Telmisartan

Following either intravenous or oral administration of ^14C-labeled telmisartan, most of the administered dose (>97%) was eliminated unchanged in feces via biliary excretion; only minute amounts were found in the urine (0.91% and 0.49% of total radioactivity, respectively).

Telmisartan is metabolized by conjugation to form a pharmacologically inactive acylglucuronide; the glucuronide of the parent compound is the only metabolite that has been identified in human plasma and urine. After a single dose, the glucuronide represents approximately 11% of the measured radioactivity in plasma. The cytochrome P450 isoenzymes are not involved in the metabolism of telmisartan.

Total plasma clearance of telmisartan is >800 mL/min. Terminal half-life and total clearance appear to be independent of dose.

Hydrochlorothiazide

Hydrochlorothiazide is not metabolized but is eliminated rapidly by the kidney. At least 61% of the oral dose is eliminated as unchanged drug within 24 hours.

Distribution

Telmisartan

Telmisartan is highly bound to plasma proteins (>99.5%), mainly albumin and α1-acid glycoprotein. Plasma protein binding is constant over the concentration range achieved with recommended doses. The volume of distribution for telmisartan is approximately 500 liters, indicating additional tissue binding.

Hydrochlorothiazide

Hydrochlorothiazide crosses the placental but not the blood-brain barrier and is excreted in breast milk.

Special Populations

Pediatric: Telmisartan pharmacokinetics have not been investigated in patients <18 years of age.

Geriatric: The pharmacokinetics of telmisartan do not differ between the elderly and those younger than 65 years (see DOSAGE AND ADMINISTRATION).

Gender: Plasma concentrations of telmisartan are generally 2-3 times higher in females than in males. In clinical trials, however, no significant increases in blood pressure response or in the incidence of orthostatic hypotension were found in women. No dosage adjustment is necessary.

Renal Insufficiency: Renal excretion does not contribute to the clearance of telmisartan. Based on modest experience in patients with mild-to-moderate renal impairment (creatinine clearance of 30-80 mL/min, mean clearance approximately 50 mL/min), no dosage adjustment is necessary in patients with decreased renal function. Telmisartan is not removed from blood by hemofiltration (see PRECAUTIONS and DOSAGE AND ADMINISTRATION).

Hepatic Insufficiency: In patients with hepatic insufficiency, plasma concentrations of telmisartan are increased, and absolute bioavailability approaches 100% (see PRECAUTIONS and DOSAGE AND ADMINISTRATION).

Drug Interactions: See PRECAUTIONS, Drug Interactions.

Pharmacodynamics

Telmisartan

In normal volunteers, a dose of telmisartan 80 mg inhibited the pressor response to an intravenous infusion of angiotensin II by about 90% at peak plasma concentrations with approximately 40% inhibition persisting for 24 hours.

Plasma concentration of angiotensin II and plasma renin activity (PRA) increased in a dose-dependent manner after single administration of telmisartan to healthy subjects and repeated administration to hypertensive patients. The once-daily administration of up to 80 mg telmisartan to healthy subjects did not influence plasma aldosterone concentrations. In multiple dose studies with hypertensive patients, there were no clinically significant changes in electrolytes (serum potassium or sodium), or in metabolic function (including serum levels of cholesterol, triglycerides, HDL, LDL, glucose, or uric acid).

In 30 hypertensive patients with normal renal function treated for 8 weeks with telmisartan 80 mg or telmisartan 80 mg in combination with hydrochlorothiazide 12.5 mg, there were no clinically significant changes from baseline in renal blood flow, glomerular filtration rate, filtration fraction, renovascular resistance, or creatinine clearance.

Hydrochlorothiazide

After oral administration of hydrochlorothiazide, diuresis begins within 2 hours, peaks in about 4 hours and lasts about 6 to 12 hours.

Clinical Trials

Telmisartan

The antihypertensive effects of telmisartan have been demonstrated in six principal placebo-controlled clinical trials, studying a range of 20-160 mg; one of these examined the antihypertensive effects of telmisartan and hydrochlorothiazide in combination. The studies involved a total of 1773 patients with mild to moderate hypertension (diastolic blood pressure of 95-114 mmHg), 1031 of whom were treated with telmisartan. Following once daily administration of telmisartan, the magnitude of blood pressure reduction from baseline after placebo subtraction was approximately (SBP/DBP) 6-8/6 mmHg for 20 mg, 9-13/6-8 mmHg for 40 mg, and 12-13/7-8 mmHg for 80 mg. Larger doses (up to 160 mg) did not appear to cause a further decrease in blood pressure.

Upon initiation of antihypertensive treatment with telmisartan, blood pressure was reduced after the first dose, with a maximal reduction by about 4 weeks. With cessation of treatment with telmisartan tablets, blood pressure gradually returned to baseline values over a period of several days to one week. During long-term studies (without placebo control) the effect of telmisartan appeared to be maintained for up to at least one year. The antihypertensive effect of telmisartan is not influenced by patient age, gender, weight or body mass index. Blood pressure response in black patients (usually a low-renin population) is noticeably less than that in Caucasian patients. This has been true for most, but not all, angiotensin II antagonists and ACE inhibitors.

The onset of antihypertensive activity occurs within 3 hours after administration of a single oral dose. At doses of 20, 40, and 80 mg, the antihypertensive effect of once daily administration of telmisartan is maintained for the full 24-hour dose interval. With automated ambulatory blood pressure monitoring and conventional blood pressure measurements, the 24-hour trough-to-peak ratio for 40-80 mg doses of telmisartan was 70-100% for both systolic and diastolic blood pressure. The incidence of symptomatic orthostasis after the first dose in all controlled trials was low (0.04%).

There were no changes in the heart rate of patients treated with telmisartan in controlled trials.

Telmisartan and Hydrochlorothiazide

In controlled clinical trials with over 2500 patients, 1017 patients were exposed to telmisartan (20 to 160 mg) and concomitant hydrochlorothiazide (6.25 to 25 mg). These trials included one factorial trial with combinations of telmisartan (20, 40, 80, 160 mg, or placebo) and hydrochlorothiazide (6.25, 12.5, 25 mg and placebo). Four other studies of at least six months duration allowed add-on of hydrochlorothiazide for patients who either were not adequately controlled on the randomized monotherapy dose or had not achieved adequate response after completing the up-titration of telmisartan.

The combination of telmisartan and hydrochlorothiazide resulted in additive placebo-adjusted decreases in systolic and diastolic blood pressure at trough of 16-21/9-11 mmHg for doses between 40/12.5 mg and 80/25 mg, compared to 9-13/7-8 mmHg for telmisartan 40 mg to 80 mg and 4/4 mmHg for hydrochlorothiazide 12.5 mg alone.

In active controlled studies, the addition of 12.5 mg hydrochlorothiazide to titrated doses of telmisartan in patients who did not achieve or maintain adequate response with telmisartan monotherapy further reduced systolic and diastolic blood pressure.

The antihypertensive effect was independent of age or gender.

There was essentially no change in heart rate in patients treated with the combination of telmisartan and hydrochlorothiazide in the placebo controlled trial.

INDICATIONS AND USAGE

Micardis® HCT (telmisartan and hydrochlorothiazide) tablets are indicated for the treatment of hypertension. This fixed dose combination is not indicated for initial therapy (see DOSAGE AND ADMINISTRATION).

CONTRAINDICATIONS

MICARDIS HCT tablets are contraindicated in patients with known hypersensitivity (e.g., anaphylaxis or angioedema) to telmisartan, hydrochlorothiazide, or any other component of this product (see ADVERSE REACTIONS).

Because of the hydrochlorothiazide component, this product is contraindicated in patients with anuria or hypersensitivity to other sulfonamide-derived drugs.

WARNINGS

Fetal Toxicity

Pregnancy Category D

Use of drugs that act on the renin-angiotensin system during the second and third trimesters of pregnancy reduces fetal renal function and increases fetal and neonatal morbidity and death. Resulting oligohydramnios can be associated with fetal lung hypoplasia and skeletal deformations. Potential neonatal adverse effects include skull hypoplasia, anuria, hypotension, renal failure, and death. When pregnancy is detected, discontinue MICARDIS HCT as soon as possible. These adverse outcomes are usually associated with use of these drugs in the second and third trimester of pregnancy. Most epidemiologic studies examining fetal abnormalities after exposure to antihypertensive use in the first trimester have not distinguished drugs affecting the renin-angiotensin system from other antihypertensive agents. Appropriate management of maternal hypertension during pregnancy is important to optimize outcomes for both mother and fetus.

In the unusual case that there is no appropriate alternative to therapy with drugs affecting the renin-angiotensin system for a particular patient, apprise the mother of the potential risk to the fetus. Perform serial ultrasound examinations to assess the intra-amniotic environment. If oligohydramnios is observed, discontinue MICARDIS HCT, unless it is considered lifesaving for the mother. Fetal testing may be appropriate, based on the week of pregnancy. Patients and physicians should be aware, however, that oligohydramnios may not appear until after the fetus has sustained irreversible injury. Closely observe infants with histories of in utero exposure to MICARDIS HCT for hypotension, oliguria, and hyperkalemia (see PRECAUTIONS, Pediatric Use).

No teratogenic effects were observed when telmisartan was administered to pregnant rats at oral doses of up to 50 mg/kg/day and to pregnant rabbits at oral doses up to 45 mg/kg/day. In rabbits, embryolethality associated with maternal toxicity (reduced body weight gain and food consumption) was observed at 45 mg/kg/day [about 12 times the maximum recommended human dose (MRHD) of 80 mg on a mg/m^2 basis]. In rats, maternally toxic (reduction in body weight gain and food consumption) telmisartan doses of 15 mg/kg/day (about 1.9 times the MRHD on a mg/m^2 basis), administered during late gestation and lactation, were observed to produce adverse effects in neonates, including reduced viability, low birth weight, delayed maturation, decreased weight gain. Telmisartan has been shown to be present in rat fetuses during late gestation and in rat milk. The no observed effect doses for developmental toxicity in rats and rabbits, 5 and 15 mg/kg/day, respectively, are about 0.64 and 3.7 times, on a mg/m^2 basis, the maximum recommended human dose of telmisartan (80 mg/day).

Studies in which hydrochlorothiazide was administered to pregnant mice and rats during their periods of major organogenesis at doses up to 3000 and 1000 mg/kg/day, respectively, provided no evidence of harm to the fetus.

Thiazides cross the placental barrier and appear in cord blood. There is a risk of fetal or neonatal jaundice, thrombocytopenia, and possibly other adverse reactions that have occurred in adults.

Hypotension in Volume-Depleted Patients

Initiation of antihypertensive therapy in patients whose renin-angiotensin system are activated such as patients who are intravascular volume- or sodium-depleted, e.g., in patients treated vigorously with diuretics, should only be approached cautiously. These conditions should be corrected prior to administration of Micardis® HCT (telmisartan and hydrochlorothiazide) tablets. Treatment should be started under close medical supervision (see DOSAGE AND ADMINISTRATION). If hypotension occurs, the patients should be placed in the supine position and, if necessary, given an intravenous infusion of normal saline. A transient hypotensive response is not a contraindication to further treatment which usually can be continued without difficulty once the blood pressure has stabilized.

Hydrochlorothiazide

Hepatic Impairment: Thiazide diuretics should be used with caution in patients with impaired hepatic function or progressive liver disease, since minor alterations of fluid and electrolyte balance may precipitate hepatic coma.

Hypersensitivity Reaction: Hypersensitivity reactions to hydrochlorothiazide may occur in patients with or without a history of allergy or bronchial asthma, but are more likely in patients with such a history.

Systemic Lupus Erythematosus: Thiazide diuretics have been reported to cause exacerbation or activation of systemic lupus erythematosus.

Lithium Interaction: Lithium generally should not be given with thiazides (see PRECAUTIONS, Drug Interactions, Hydrochlorothiazide, Lithium).

Acute Myopia and Secondary Angle-Closure Glaucoma: Hydrochlorothiazide, a sulfonamide, can cause an idiosyncratic reaction, resulting in acute transient myopia and acute angle-closure glaucoma. Symptoms include acute onset of decreased visual acuity or ocular pain and typically occur within hours to weeks of drug initiation. Untreated angle-closure glaucoma can lead to permanent vision loss. The primary treatment is to discontinue hydrochlorothiazide as rapidly as possible. Prompt medical or surgical treatments may need to be considered if the intraocular pressure remains uncontrolled. Risk factors for developing acute angle-closure glaucoma may include a history of sulfonamide or penicillin allergy.

PRECAUTIONS

Serum Electrolytes

Telmisartan and Hydrochlorothiazide

In controlled trials using the telmisartan/hydrochlorothiazide combination treatment, no patient administered 40/12.5 mg, 80/12.5 mg or 80/25 mg had a decrease in potassium ≥1.4 mEq/L, and no patient experienced hyperkalemia. No discontinuations due to hypokalemia occurred during treatment with the telmisartan/hydrochlorothiazide combination. The absence of significant changes in serum potassium levels may be due to the opposing mechanisms of action of telmisartan and hydrochlorothiazide on potassium excretion on the kidney.

Hydrochlorothiazide

Periodic determinations of serum electrolytes to detect possible electrolyte imbalance should be performed at appropriate intervals. All patients receiving thiazide therapy should be observed for clinical signs of fluid or electrolyte imbalance: hyponatremia, hypochloremic alkalosis, and hypokalemia. Serum and urine electrolyte determinations are particularly important when the patient experiences excessive vomiting or receives parenteral fluids. Warning signs or symptoms of fluid and electrolyte imbalance, irrespective of cause, include dryness of mouth, thirst, weakness, lethargy, drowsiness, restlessness, confusion, seizures, muscle pains or cramps, muscular fatigue, hypotension, oliguria, tachycardia, and gastrointestinal disturbances such as nausea and vomiting.

Hypokalemia may develop, especially with brisk diuresis, when severe cirrhosis is present, or after prolonged therapy.

Interference with adequate oral electrolyte intake will also contribute to hypokalemia. Hypokalemia may cause cardiac arrhythmia and may also sensitize or exaggerate the response of the heart to the toxic effects of digitalis (e.g., increased ventricular irritability).

Although any chloride deficit is generally mild and usually does not require specific treatment except under extraordinary circumstances (as in liver disease or renal disease), chloride replacement may be required in the treatment of metabolic alkalosis.

Dilutional hyponatremia may occur in edematous patients in hot weather; appropriate therapy is water restriction, rather than administration of salt except in rare instances when the hyponatremia is life-threatening. In actual salt depletion, appropriate replacement is the therapy of choice.

Hyperuricemia may occur or frank gout may be precipitated in certain patients receiving thiazide therapy.

In diabetic patients dosage adjustments of insulin or oral hypoglycemic agents may be required. Hyperglycemia may occur with thiazide diuretics. Thus latent diabetes mellitus may become manifest during thiazide therapy.

The antihypertensive effects of the drug may be enhanced in the post sympathectomy patient.

If progressive renal impairment becomes evident consider withholding or discontinuing diuretic therapy.

Thiazides have been shown to increase the urinary excretion of magnesium; this may result in hypomagnesemia.

Thiazides may decrease urinary calcium excretion. Thiazides may cause intermittent and slight elevation of serum calcium in the absence of known disorders of calcium metabolism. Marked hypercalcemia may be evidence of hidden hyperparathyroidism. Thiazides should be discontinued before carrying out tests for parathyroid function.

Increases in cholesterol and triglyceride levels may be associated with thiazide diuretic therapy.

Impaired Hepatic Function

Telmisartan

As the majority of telmisartan is eliminated by biliary excretion, patients with biliary obstructive disorders or hepatic insufficiency can be expected to have reduced clearance. Micardis® HCT (telmisartan and hydrochlorothiazide) tablets should therefore be used with caution in these patients.

Impaired Renal Function

Telmisartan

As a consequence of inhibiting the renin-angiotensin-aldosterone system, changes in renal function may be anticipated in susceptible individuals. In patients whose renal function may depend on the activity of the renin-angiotensin-aldosterone system (e.g., patients with severe congestive heart failure), treatment with angiotensin-converting enzyme inhibitors and angiotensin receptor antagonists has been associated with oliguria and/or progressive azotemia and (rarely) with acute renal failure and/or death. Similar results may be anticipated in patients treated with telmisartan.

In studies of ACE inhibitors in patients with unilateral or bilateral renal artery stenosis, increases in serum creatinine or blood urea nitrogen were observed. There has been no long-term use of telmisartan in patients with unilateral or bilateral renal artery stenosis but an effect similar to that seen with ACE inhibitors should be anticipated.

Hydrochlorothiazide

Thiazides should be used with caution in severe renal disease. In patients with renal disease, thiazides may precipitate azotemia. Cumulative effects of the drug may develop in patients with impaired renal function.

Dual Blockade of the Renin-angiotensin-aldosterone System

Telmisartan

As a consequence of inhibiting the renin-angiotensin-aldosterone system, changes in renal function (including acute renal failure) have been reported. Dual blockade of the renin-angiotensin-aldosterone system (e.g., by adding an ACE-inhibitor to an angiotensin II receptor antagonist) should include close monitoring of renal function.

The ONTARGET trial enrolled 25,620 patients >55 years old with atherosclerotic disease or diabetes with end-organ damage, randomized them to telmisartan only, ramipril only, or the combination, and followed them for a median of 56 months. Patients receiving the combination of telmisartan and ramipril did not obtain any additional benefit on the composite endpoint of cardiovascular death, myocardial infarction, stroke and heart failure hospitalization compared to monotherapy, but experienced an increased incidence of clinically important renal dysfunction (e.g., acute renal failure) compared with groups receiving telmisartan alone or ramipril alone.

Co-administration of telmisartan and ramipril increases the exposure to both ramipril and ramiprilat by a factor of about 2 (see PRECAUTIONS, Drug Interactions).

Concomitant use of telmisartan and ramipril is not recommended.

Information for Patients

Pregnancy: Female patients of childbearing age should be told about the consequences of exposure to MICARDIS HCT during pregnancy. Discuss treatment options with women planning to become pregnant. Patients should be asked to report pregnancies to their physicians as soon as possible.

Symptomatic Hypotension: A patient receiving Micardis® HCT (telmisartan and hydrochlorothiazide) tablets should be cautioned that lightheadedness can occur, especially during the first days of therapy, and that it should be reported to the prescribing physician. The patients should be told that if syncope occurs, MICARDIS HCT tablets should be discontinued until the physician has been consulted.

All patients should be cautioned that inadequate fluid intake, excessive perspiration, diarrhea, or vomiting can lead to an excessive fall in blood pressure, with the same consequences of lightheadedness and possible syncope.

Potassium Supplements: A patient receiving MICARDIS HCT tablets should be told not to use potassium supplements or salt substitutes that contain potassium without consulting the prescribing physician.

Drug Interactions

Telmisartan

Digoxin: When telmisartan was co-administered with digoxin, median increases in digoxin peak plasma concentration (49%) and in trough concentration (20%) were observed. It is, therefore, recommended that digoxin levels be monitored when initiating, adjusting, and discontinuing telmisartan to avoid possible over- or under-digitalization.

Lithium: Reversible increases in serum lithium concentrations and toxicity have been reported during concomitant administration of lithium with angiotensin converting enzyme inhibitors. Cases have also been reported with angiotensin II receptor antagonists including telmisartan. Because lithium should not be used with diuretics, the use of lithium with telmisartan and hydrochlorothiazide is not recommended.

Non-Steroidal Anti-Inflammatory Agents including Selective Cyclooxygenase-2 Inhibitors (COX-2 Inhibitors): In patients who are elderly, volume-depleted (including those on diuretic therapy), or with compromised renal function, co-administration of NSAIDs, including selective COX-2 inhibitors, with angiotensin II receptor antagonists, including telmisartan, may result in deterioration of renal function, including possible acute renal failure. These effects are usually reversible. Monitor renal function periodically in patients receiving telmisartan and NSAID therapy.

The antihypertensive effect of angiotensin II receptor antagonists, including telmisartan may be attenuated by NSAIDs including selective COX-2 inhibitors.

Ramipril and Ramiprilat: Co-administration of telmisartan 80 mg once daily and ramipril 10 mg once daily to healthy subjects increases steady-state Cmax and AUC of ramipril 2.3 and 2.1 fold, respectively, and Cmax and AUC of ramiprilat 2.4 and 1.5 fold, respectively. In contrast, Cmax and AUC of telmisartan decrease by 31% and 16%, respectively. When co-administering telmisartan and ramipril, the response may be greater because of the possibly additive pharmacodynamic effects of the combined drugs, and also because of the increased exposure to ramipril and ramiprilat in the presence of telmisartan.

Warfarin: Telmisartan administered for 10 days slightly decreased the mean warfarin trough plasma concentration; this decrease did not result in a change in International Normalized Ratio (INR).

Other Drugs: Co-administration of telmisartan did not result in a clinically significant interaction with acetaminophen, amlodipine, glibenclamide, simvastatin, hydrochlorothiazide or ibuprofen. Telmisartan is not metabolized by the cytochrome P450 system and had no effects in vitro on cytochrome P450 enzymes, except for some inhibition of CYP2C19. Telmisartan is not expected to interact with drugs that inhibit cytochrome P450 enzymes; it is also not expected to interact with drugs metabolized by cytochrome P450 enzymes, except for possible inhibition of the metabolism of drugs metabolized by CYP2C19.

Hydrochlorothiazide

When administered concurrently, the following drugs may interact with thiazide diuretics:

Alcohol, barbiturates, or narcotics: Potentiation of orthostatic hypotension may occur.

Antidiabetic drugs (oral agents and insulin): Dosage adjustment of the antidiabetic drug may be required.

Other antihypertensive drugs: Additive effect or potentiation.

Cholestyramine and colestipol resins: Absorption of hydrochlorothiazide is impaired in the presence of anionic exchange resins. Single doses of either cholestyramine or colestipol resins bind the hydrochlorothiazide and reduce its absorption from the gastrointestinal tract by up to 85% and 43%, respectively.

Corticosteroids, ACTH: Intensified electrolyte depletion, particularly hypokalemia.

Pressor amines (e.g., norepinephrine): Possible decreased response to pressor amines but not sufficient to preclude their use.

Skeletal muscle relaxants, nondepolarizing (e.g., tubocurarine): Possible increased responsiveness to the muscle relaxant.

Lithium: Should not generally be given with diuretics. Diuretic agents reduce the renal clearance of lithium and add a high risk of lithium toxicity. Refer to the package insert for lithium preparations before use of such preparations with Micardis® HCT (telmisartan and hydrochlorothiazide) tablets.

Non-steroidal anti-inflammatory drugs: In some patients, the administration of a non-steroidal anti-inflammatory agent can reduce the diuretic, natriuretic, and antihypertensive effects of loop, potassium-sparing and thiazide diuretics. Therefore, when MICARDIS HCT tablets and non-steroidal anti-inflammatory agents are used concomitantly, the patient should be observed closely to determine if the desired effect of the diuretic is obtained.

Carcinogenesis, Mutagenesis, Impairment of Fertility

Telmisartan and Hydrochlorothiazide

No carcinogenicity, mutagenicity, or fertility studies have been conducted with the combination of telmisartan and hydrochlorothiazide.

Telmisartan

There was no evidence of carcinogenicity when telmisartan was administered in the diet to mice and rats for up to 2 years. The highest doses administered to mice (1000 mg/kg/day) and rats (100 mg/kg/day) are, on a mg/m^2 basis, about 59 and 13 times, respectively, the maximum recommended human dose (MRHD) of telmisartan. These same doses have been shown to provide average systemic exposures to telmisartan >100 times and >25 times, respectively, the systemic exposure in humans receiving the MRHD (80 mg/day).

Genotoxicity assays did not reveal any telmisartan-related effects at either the gene or chromosome level. These assays included bacterial mutagenicity tests with Salmonella and E. coli (Ames), a gene mutation test with Chinese hamster V79 cells, a cytogenetic test with human lymphocytes, and a mouse micronucleus test.

No drug-related effects on the reproductive performance of male and female rats were noted at 100 mg/kg/day (the highest dose administered), about 13 times, on a mg/m^2 basis, the MRHD of telmisartan. This dose in the rat resulted in an average systemic exposure (telmisartan AUC as determined on day 6 of pregnancy) at least 50 times the average systemic exposure in humans at the MRHD (80 mg/day).

Hydrochlorothiazide

Two-year feeding studies in mice and rats conducted under the auspices of the National Toxicology Program (NTP) uncovered no evidence of a carcinogenic potential of hydrochlorothiazide in female mice (at doses of up to approximately 600 mg/kg/day) or in male and female rats (at doses of up to approximately 100 mg/kg/day). The NTP, however, found equivocal evidence for hepatocarcinogenicity in male mice.

Hydrochlorothiazide was not genotoxic in vitro in the Ames mutagenicity assay of Salmonella typhimurium strains TA 98, TA 100, TA 1535, TA 1537, and TA 1538 and in the Chinese Hamster Ovary (CHO) test for chromosomal aberrations, or in vivo in assays using mouse germinal cell chromosomes, Chinese hamster bone marrow chromosomes, and the Drosophila sex-linked recessive lethal trait gene. Positive test results were obtained in the in vitro CHO Sister Chromatid Exchange (clastogenicity) assay, in the Mouse Lymphoma Cell (mutagenicity) assay, and in the Aspergillus nidulans non-disjunction assay.

Hydrochlorothiazide had no adverse effects on the fertility of mice and rats of either sex in studies wherein these species were exposed, via their diet, to doses of up to 100 and 4 mg/kg, respectively, prior to mating and throughout gestation.

Nursing Mothers

It is not known whether telmisartan is excreted in human milk, but telmisartan was shown to be present in the milk of lactating rats. Thiazides appear in human milk. Because of the potential for adverse effects on the nursing infant, a decision should be made whether to discontinue nursing or discontinue the drug, taking into account the importance of the drug to the mother.

Pediatric Use

Neonates with a history of in utero exposure to MICARDIS HCT:
If oliguria or hypotension occurs, direct attention toward support of blood pressure and renal perfusion. Exchange transfusions or dialysis may be required as a means of reversing hypotension and/or substituting for disordered renal function.

Safety and effectiveness in pediatric patients have not been established.

Geriatric Use

In the controlled clinical trials (n=1017), approximately 20% of patients treated with telmisartan/hydrochlorothiazide were 65 years of age or older, and 5% were 75 years of age or older. No overall differences in effectiveness and safety of telmisartan/hydrochlorothiazide were observed in these patients compared to younger patients. Other reported clinical experience has not identified differences in responses between the elderly and younger patients, but greater sensitivity of some older individuals cannot be ruled out.

ADVERSE REACTIONS

Micardis® HCT (telmisartan and hydrochlorothiazide) tablets has been evaluated for safety in over 1700 patients, including 716 treated for over six months and 420 for over one year. In clinical trials with MICARDIS HCT tablets, no unexpected adverse events have been observed. Adverse experiences have been limited to those that have been previously reported with telmisartan and/or hydrochlorothiazide. The overall incidence of adverse experiences reported with the combination was comparable to placebo. Most adverse experiences were mild in intensity and transient in nature and did not require discontinuation of therapy.

Adverse events occurring at an incidence of 2% or more in patients treated with telmisartan/hydrochlorothiazide and at a greater rate than in patients treated with placebo, irrespective of their causal association, are presented in Table 1.

TABLE 1 Adverse Events Occurring in ≥ 2% of Telmisartan/Hydrochlorothiazide (HCTZ) Patients*
 | Telm/HCTZ | Placebo | Telm | HCTZ
 | (N=414) | (N=74) | (N=209) | (N=121)
 | (%) | (%) | (%) | (%)
Body as a whole
Fatigue | 3 | 1 | 3 | 3
Influenza-like symptoms | 2 | 1 | 2 | 3
Central/peripheral nervous system
Dizziness | 5 | 1 | 4 | 6
Gastrointestinal system
Diarrhea | 3 | 0 | 5 | 2
Nausea | 2 | 0 | 1 | 2
Respiratory system disorder
Sinusitis | 4 | 3 | 3 | 6
Upper respiratory tract infection | 8 | 7 | 7 | 10
* includes all doses of telmisartan (20-160 mg), hydrochlorothiazide (6.25-25 mg), and combinations thereof

The following adverse events were reported at a rate less than 2% in patients treated with telmisartan/hydrochlorothiazide and at a greater rate than in patients treated with placebo: back pain, dyspepsia, vomiting, tachycardia, hypokalemia, bronchitis, pharyngitis, rash, hypotension postural, abdominal pain.

Finally, the following adverse events were reported at a rate of 2% or greater in patients treated with telmisartan/hydrochlorothiazide, but were as, or more common in the placebo group: pain, headache, cough, urinary tract infection.

Adverse events occurred at approximately the same rates in men and women, older and younger patients, and black and non-black patients.

In controlled trials (n=1017), 0.3% of patients treated with Micardis® HCT (telmisartan and hydrochlorothiazide) tablets 40/12.5 mg, 80/12.5 mg or 80/25 mg discontinued due to orthostatic hypotension, and the incidence of dizziness was 4%, 7%, and 1%, respectively.

Telmisartan

Other adverse experiences that have been reported with telmisartan, without regard to causality, are listed below:

Autonomic Nervous System: impotence, increased sweating, flushing

Body as a Whole: allergy, fever, leg pain, malaise, chest pain

Cardiovascular: palpitation, dependent edema, angina pectoris, leg edema, abnormal ECG, hypertension, peripheral edema

CNS: insomnia, somnolence, migraine, vertigo, paresthesia, involuntary muscle contractions, hypoaesthesia

Gastrointestinal: flatulence, constipation, gastritis, dry mouth, hemorrhoids, gastroenteritis, enteritis, gastroesophageal reflux, toothache, non-specific gastrointestinal disorders

Metabolic: gout, hypercholesterolemia, diabetes mellitus

Musculoskeletal: arthritis, arthralgia, leg cramps, myalgia

Psychiatric: anxiety, depression, nervousness

Resistance Mechanism: infection, fungal infection, abscess, otitis media

Respiratory: asthma, rhinitis, dyspnea, epistaxis

Skin: dermatitis, eczema, pruritus

Urinary: micturition frequency, cystitis

Vascular: cerebrovascular disorder

Special Senses: abnormal vision, conjunctivitis, tinnitus, earache

A single case of angioedema was reported (among a total of 3781 patients treated with telmisartan).

Hydrochlorothiazide

Other adverse experiences that have been reported with hydrochlorothiazide, without regard to causality, are listed below:

Body as a whole: weakness

Digestive: pancreatitis, jaundice (intrahepatic cholestatic jaundice), sialadenitis, cramping, gastric irritation

Hematologic: aplastic anemia, agranulocytosis, leukopenia, hemolytic anemia, thrombocytopenia

Hypersensitivity: purpura, photosensitivity, urticaria, necrotizing angiitis (vasculitis and cutaneous vasculitis), fever, respiratory distress including pneumonitis and pulmonary edema, anaphylactic reactions

Metabolic: hyperglycemia, glycosuria, hyperuricemia

Musculoskeletal: muscle spasm

Nervous System/Psychiatric: restlessness

Renal: renal failure, renal dysfunction, interstitial nephritis

Skin: erythema multiforme including Stevens-Johnson syndrome, exfoliative dermatitis including toxic epidermal necrolysis

Special Senses: transient blurred vision, xanthopsia

Post-Marketing Experience

The following adverse reactions have been identified during post-approval use of Micardis® (telmisartan) tablets. Because these reactions are reported voluntarily from a population of uncertain size, it is not always possible to estimate reliably their frequency or establish a causal relationship to drug exposure. Decisions to include these reactions in labeling are typically based on one or more of the following factors: (1) seriousness of the reaction, (2) frequency of reporting, or (3) strength of causal connection to MICARDIS tablets. The most frequently spontaneously reported events include: headache, dizziness, asthenia, coughing, nausea, fatigue, weakness, edema, face edema, lower limb edema, angioneurotic edema, urticaria, hypersensitivity, sweating increased, erythema, chest pain, atrial fibrillation, congestive heart failure, myocardial infarction, blood pressure increased, hypertension aggravated, hypotension (including postural hypotension), hyperkalemia, syncope, dyspepsia, diarrhea, pain, urinary tract infection, erectile dysfunction, back pain, abdominal pain, muscle cramps (including leg cramps), myalgia, bradycardia, eosinophilia, thrombocytopenia, uric acid increased, abnormal hepatic function/liver disorder, renal impairment including acute renal failure, anemia, increased CPK, anaphylactic reaction, tendon pain (including tendonitis, tenosynovitis), drug eruption (toxic skin eruption mostly reported as toxicoderma, rash, and urticaria), hypoglycemia (in diabetic patients), and angioedema (with fatal outcome).

Rare cases of rhabdomyolysis have been reported in patients receiving angiotensin II receptor blockers, including MICARDIS tablets.

Clinical Laboratory Findings

In controlled trials, clinically relevant changes in standard laboratory test parameters were rarely associated with administration of Micardis® HCT (telmisartan and hydrochlorothiazide) tablets.

Hemoglobin and Hematocrit: Decreases in hemoglobin (≥ 2 g/dL) and hematocrit (≥ 9%) were observed in 1.2% and 0.6% of telmisartan/hydrochlorothiazide patients, respectively, in controlled trials. Changes in hemoglobin and hematocrit were not considered clinically significant and there were no discontinuations due to anemia.

Creatinine, Blood Urea Nitrogen (BUN): Increases in BUN (≥ 11.2 mg/dL) and serum creatinine (≥ 0.5 mg/dL) were observed in 2.8% and 1.4%, respectively, of patients with essential hypertension treated with MICARDIS HCT tablets in controlled trials. No patient discontinued treatment with MICARDIS HCT tablets due to an increase in BUN or creatinine.

Liver Function Tests: Occasional elevations of liver enzymes and/or serum bilirubin have occurred. No telmisartan/hydrochlorothiazide treated patients discontinued therapy due to abnormal hepatic function.

Serum Electrolytes: See PRECAUTIONS.

OVERDOSAGE

Telmisartan

Limited data are available with regard to overdosage in humans. The most likely manifestations of overdosage with telmisartan would be hypotension, dizziness and tachycardia; bradycardia could occur from parasympathetic (vagal) stimulation. If symptomatic hypotension should occur, supportive treatment should be instituted. Telmisartan is not removed by hemodialysis.

Hydrochlorothiazide

The most common signs and symptoms observed in patients are those caused by electrolyte depletion (hypokalemia, hypochloremia, hyponatremia) and dehydration resulting from excessive diuresis. If digitalis has also been administered, hypokalemia may accentuate cardiac arrhythmias. The degree to which hydrochlorothiazide is removed by hemodialysis has not been established. The oral LD50 of hydrochlorothiazide is greater than 10 g/kg in both mice and rats.

DOSAGE AND ADMINISTRATION

The usual starting dose of telmisartan is 40 mg once a day; blood pressure response is dose related over the range of 20-80 mg. Patients with depletion of intravascular volume should have the condition corrected or telmisartan tablets should be initiated under close medical supervision (see WARNINGS, Hypotension in Volume-Depleted Patients). Patients with biliary obstructive disorders or hepatic insufficiency should have treatment started under close medical supervision (see PRECAUTIONS).

Hydrochlorothiazide is effective in doses of 12.5 mg to 50 mg once daily.

To minimize dose-independent side effects, it is usually appropriate to begin combination therapy only after a patient has failed to achieve the desired effect with monotherapy. The side effects (see WARNINGS) of telmisartan are generally rare and apparently independent of dose; those of hydrochlorothiazide are a mixture of dose-dependent phenomena (primarily hypokalemia) and dose-independent phenomena (e.g., pancreatitis), the former much more common than the latter. Therapy with any combination of telmisartan and hydrochlorothiazide will be associated with both sets of dose-independent side effects.

Micardis® HCT (telmisartan and hydrochlorothiazide) tablets may be administered with other antihypertensive agents.

MICARDIS HCT tablets may be administered with or without food.

Replacement Therapy

The combination may be substituted for the titrated components.

Dose Titration by Clinical Effect

MICARDIS HCT tablets are available as tablets containing either telmisartan 40 mg and hydrochlorothiazide 12.5 mg, or telmisartan 80 mg and hydrochlorothiazide 12.5 mg or 25 mg. A patient whose blood pressure is not adequately controlled with telmisartan monotherapy 80 mg (see above) may be switched to MICARDIS HCT tablets, telmisartan 80 mg/hydrochlorothiazide 12.5 mg once daily, and finally titrated up to 160/25 mg, if necessary.

A patient whose blood pressure is inadequately controlled by 25 mg once daily of hydrochlorothiazide may be switched to MICARDIS HCT (telmisartan 80 mg/hydrochlorothiazide 12.5 mg or telmisartan 80 mg/hydrochlorothiazide 25 mg) tablets once daily. The clinical response to MICARDIS HCT tablets should be subsequently evaluated and if blood pressure remains uncontrolled after 2-4 weeks of therapy, the dose may be titrated up to 160/25 mg, if necessary. Those patients controlled by 25 mg hydrochlorothiazide but who experience hypokalemia with this regimen, may be switched to MICARDIS HCT (telmisartan 80 mg/hydrochlorothiazide 12.5 mg) tablets once daily, reducing the dose of hydrochlorothiazide without reducing the overall expected antihypertensive response.

Patients with Renal Impairment

The usual regimens of therapy with Micardis® HCT (telmisartan and hydrochlorothiazide) tablets may be followed as long as the patient’s creatinine clearance is >30 mL/min. In patients with more severe renal impairment, loop diuretics are preferred to thiazides, so MICARDIS HCT tablets are not recommended.

Patients with Hepatic Impairment

MICARDIS HCT tablets are not recommended for patients with severe hepatic impairment. Patients with biliary obstructive disorders or hepatic insufficiency should have treatment started under close medical supervision using the 40/12.5 mg combination (see PRECAUTIONS).

HOW SUPPLIED

MICARDIS HCT tablets are available in three strengths as biconvex two-layered, oblong-shaped, uncoated tablets in three combinations of 40 mg/12.5 mg, 80 mg/12.5 mg and 80 mg/25 mg telmisartan and hydrochlorothiazide, respectively. The hydrochlorothiazide layer is red in the 40 mg/12.5 mg and 80 mg/12.5 mg tablets, and yellow in the 80 mg/25 mg tablets, and all are unmarked. The telmisartan layer for all three strengths is white, but may contain red specks in the 40 mg/12.5 mg and 80 mg/12.5 mg tablets and yellow specks in the 80 mg/25 mg tablets. The telmisartan layer is marked with the Boehringer Ingelheim logo and H4 for the 40 mg/12.5 mg dose strength, H8 for the 80 mg/12.5 mg dose strength and H9 for the 80 mg/25 mg dose strength.

Tablets are provided as follows:

MICARDIS HCT tablets 40 mg/12.5 mg are individually blister-sealed in cartons of 30 tablets as 3 x 10 cards (NDC 54868-5418-0).

MICARDIS HCT tablets 80 mg/12.5 mg are individually blister-sealed in cartons of 30 tablets as 3 x 10 cards (NDC 54868-4540-1), and individually blister-sealed in cartons of 90 tablets as 9 x 10 cards (NDC 54868-4540-2).

MICARDIS HCT tablets 80 mg/25 mg are individually blister-sealed in cartons of 30 tablets as 3 x 10 cards (NDC 54868-5297-0).

Storage

Store at 25°C (77°F); excursions permitted to 15°-30°C (59°-86°F) [see USP Controlled Room Temperature]. Tablets should not be removed from blisters until immediately before administration.

Address medical inquiries to (800) 542-6257 or (800) 459-9906 TTY.

Distributed by: Boehringer Ingelheim Pharmaceuticals, Inc.,
Ridgefield, CT 06877 USA

Licensed from: Boehringer Ingelheim International GmbH,
Ingelheim, Germany

Copyright 2012 Boehringer Ingelheim International GmbH
ALL RIGHTS RESERVED

Revised: January 2012

IT13006NA252012
10004142/09

Additional barcode labeling by:
Physicians Total Care, Inc.
Tulsa, Oklahoma 74146

PACKAGE LABEL

Micardis HCT

80 mg/25 mg

30 Tablets

NDC 54868-5297-0

PACKAGE LABEL

Micardis HCT

40 mg/12.5 mg

30 Tablets

NDC 54868-5418-0

PACKAGE LABEL

Micardis HCT

80 mg/12.5 mg

NDC 54868-4540-2